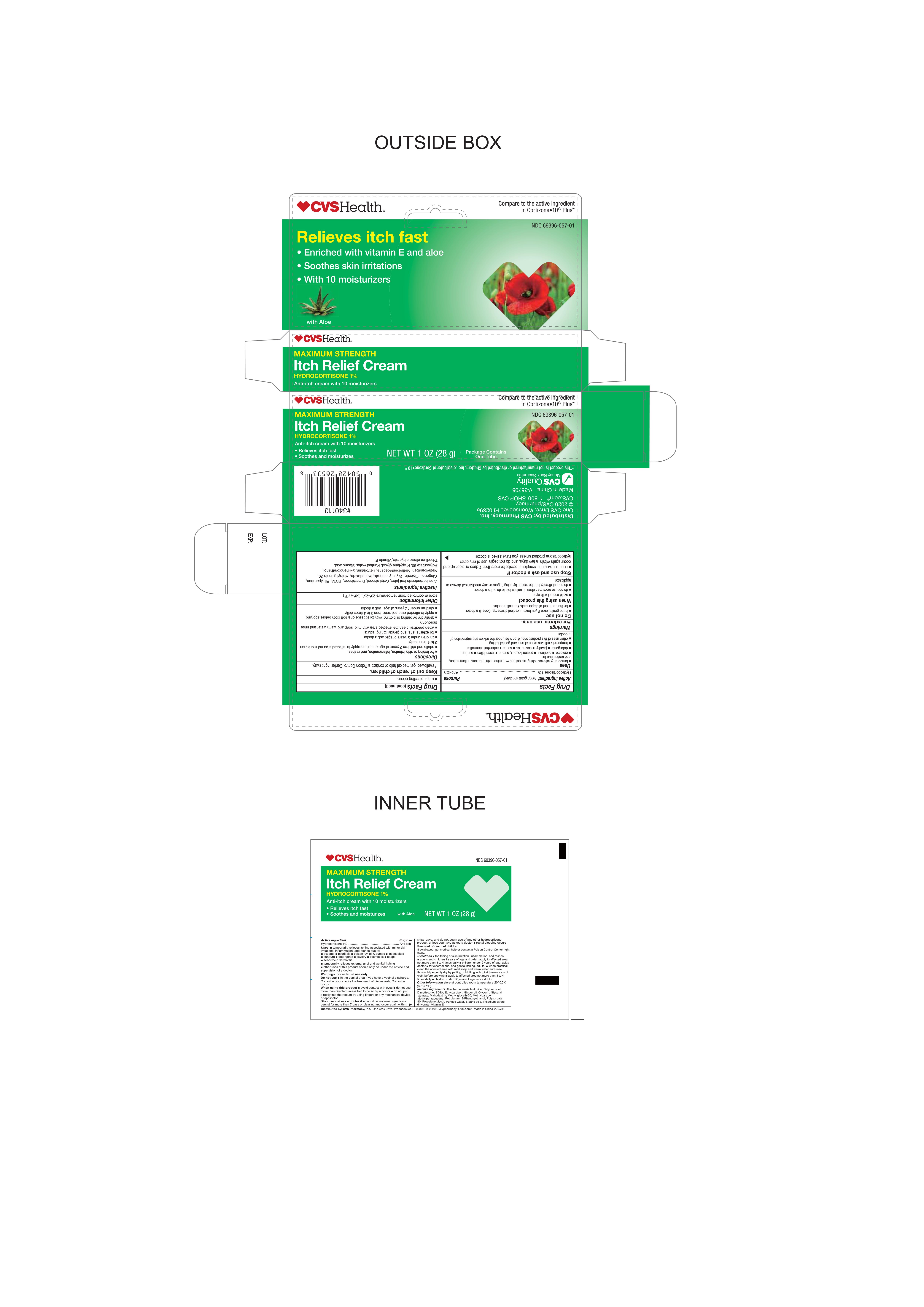 DRUG LABEL: Itch Relief
NDC: 69396-057 | Form: CREAM
Manufacturer: Trifecta Pharmaceuticals USA LLC
Category: otc | Type: HUMAN OTC DRUG LABEL
Date: 20241220

ACTIVE INGREDIENTS: HYDROCORTISONE 1 g/100 g
INACTIVE INGREDIENTS: 3-METHYLPENTADECANE; DIMETHICONE; PHENOXYETHANOL; PROPYLENE GLYCOL; ALOE VERA LEAF; METHYLPARABEN; GLYCERYL MONOSTEARATE; PETROLATUM; WATER; STEARIC ACID; TRISODIUM CITRATE DIHYDRATE; .ALPHA.-TOCOPHEROL; GLYCERIN; GINGER OIL; MALTODEXTRIN; CETYL ALCOHOL; EDETIC ACID; METHYL GLUCETH-20; ETHYLPARABEN; POLYSORBATE 80

CVS Health Itch Relief Cream

Active Ingredient

Hydrocortisone 1%

Purpose

Anti-itch

Keep out of Reach of Children

If Swallowed, get medical help or contact a Poison Control Center right away.

Uses

For temporary relief of itching associated with minor skin irritataions, inflammation and rashes due to

- Eczema
- Insect bites
- poison ivy
- poison oak
- poison sumac
- soaps
- detergents
- cosmetics
- jewelry
- seborrheic dermatitis
- psoriasis
- sunburn
- temporarily relieves external anal and genital itching.

Other uses of this product should be only under the advice and supervision of a doctor

Warnings

For External Use Only

Do not use

- In the genital area if you have a vaginal discharge.

When using this Product

- Avoid contact with the eyes.
- Do not use more than directed unless told to do so by a doctor.
- Do not put directly into rectum by using fingers or any mechanical device or applicator.

Stop Using this product and ask a doctor if

- Conditions worsen
- Symptoms persist for more than 7 days or clear up and occur again within a few days, and do not begin use of any other hydrocortisone product unless you have asked a doctor.
- Rectal bleeding occurs.

Directions

For itching or skin irritations, inflammation, and rashes.

Adults and children 2 years and older

- Apply to affected area not more than 3 to 4 times daily.

Children under 2 years of age

- ask a doctor.

For External and Anal Itching

- Adults: When practical, clean the affected area with mild soap and warm water and rinse thoroughly
- gently dry by patting or blotting with toilet tissue or a soft cloth before applying
- apply to affected area not more than 3 to 4 times daily
- Children under 12 years of age: ask a doctor

Other Information

Store at controlled room temperature 20°-25°C (68°-77°F)

Inactive Ingredients

Aloe Barbadensis leaf juice, cetyl alcohol, Dimethicone, EDTA, Ethylparaben, Ginger Oil, Glycerin, Glyceryl stearate, Maltodextrin, Methyl gluceth-20, Methylparaben, Methylpentadecane, petrolatum, 2- Phenoxyethyl alcohol, Polysorbate 80, Propylene glycol, purified water, Stearic acid, Trisodium citrate dihydrate, Vitamin E.

Questions

Call 1-800- SHOP CVS

Other Information

This product is not manufactured or distributed by Chattem Inc. distributor of Cortizone -10®

Distributed By:

CVS Pharmacy, Inc.

One CVS Drive,

Woonsocket, RI. 02895

Product of China V-36756